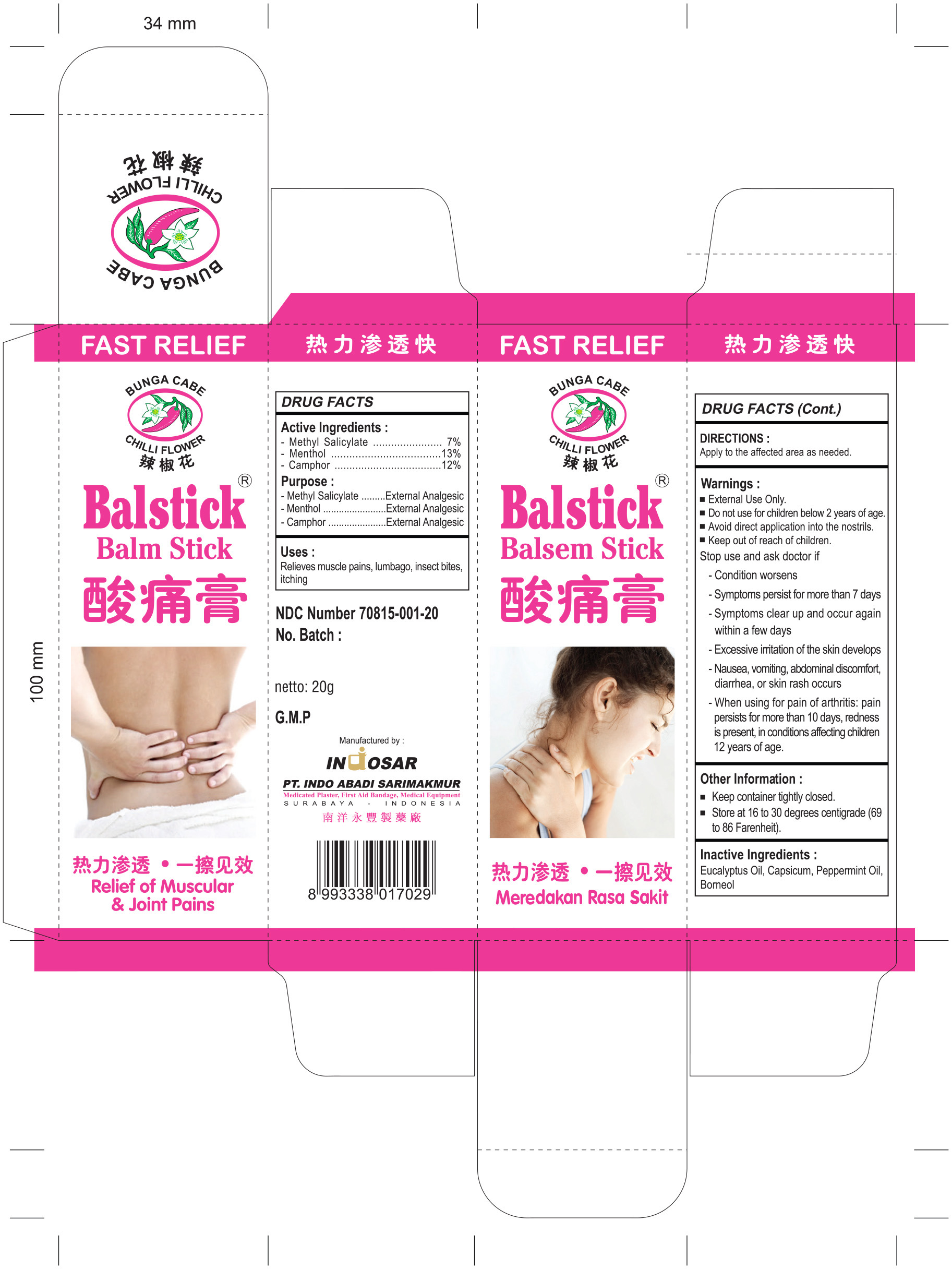 DRUG LABEL: Balm Stick
NDC: 70815-001 | Form: STICK
Manufacturer: Indo Abadi Sari Makmur, PT
Category: otc | Type: HUMAN OTC DRUG LABEL
Date: 20211227

ACTIVE INGREDIENTS: METHYL SALICYLATE 7 g/100 g; MENTHOL 13 g/100 g; CAMPHOR (SYNTHETIC) 12 g/100 g
INACTIVE INGREDIENTS: EUCALYPTUS OIL; CAPSICUM; PEPPERMINT OIL; BORNEOL

Indo Abadi Sari Makmur, PT

Active Ingredients

Methyl Salicylate 7%

Menthol 13%

Camphor 12%

Purpose

Methyl Salicylate External Analgesic

Menthol External Analgesic

Camphor External Analgesic

Uses

Relieves muscle pains, lumbago, insect bites, itching

DIRECTIONS

Apply to the affected area as needed.

Warnings

External Use Only. Do not use for children below 2 years of age. Avoid direct application into the nostrils.

Warnings

Keep out of reach of children.

Warnings

Stop use and ask doctor if

Condition worsens

Symptoms persist for more than 7 days

Symptoms clear up and occur again within a few days

Excessive irritation of the skin develops

Nausea, vomitting, abdominal discomfort, diarrhea, or skin rash occurs

When using for pain of arthritis: pain persits for more than 10 days, redness is present, in conditions affecting children 12 years of age.

Other Information

Keep container tightly closed. Store at 16 to 30 degrees centigrade (69 to 86 Farenheit).

Inactive Ingredients

Eucalyptus Oil, Capsicum, Peppermint Oil, Borneol